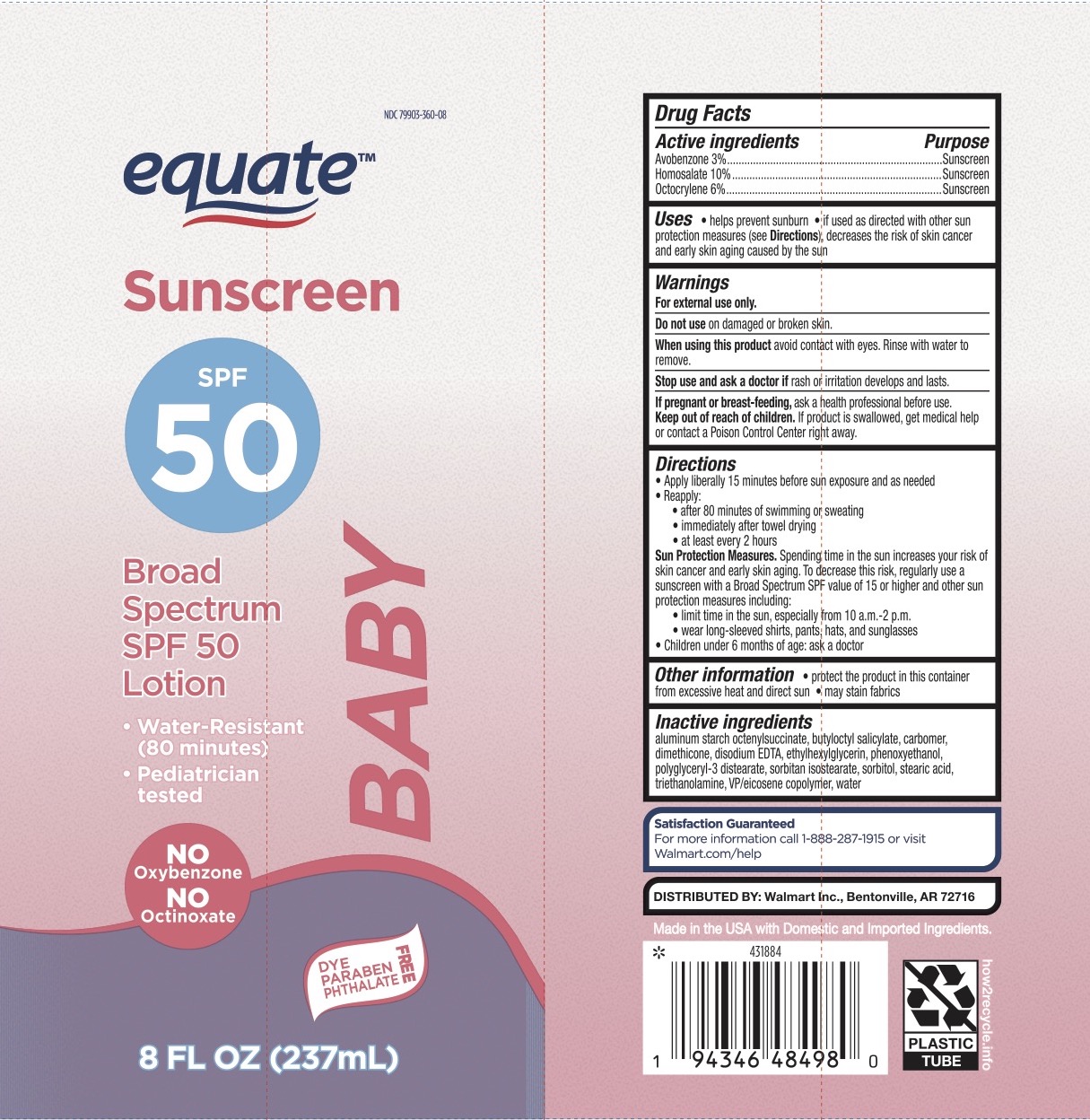 DRUG LABEL: SPF 50 Baby Sunscreen
NDC: 79903-360 | Form: LOTION
Manufacturer: Walmart Inc
Category: otc | Type: HUMAN OTC DRUG LABEL
Date: 20251222

ACTIVE INGREDIENTS: AVOBENZONE 3 g/100 mL; HOMOSALATE 10 g/100 mL; OCTOCRYLENE 6 g/100 mL
INACTIVE INGREDIENTS: SORBITAN ISOSTEARATE; SORBITOL; WATER; TROLAMINE; EICOSYL POVIDONE; STEARIC ACID; POLYGLYCERYL-3 DISTEARATE; PHENOXYETHANOL; ETHYLHEXYLGLYCERIN; ALUMINUM STARCH OCTENYLSUCCINATE; EDETATE DISODIUM; BUTYLOCTYL SALICYLATE; DIMETHICONE 20; CARBOMER 940

Equate SPF 50 Baby Sunscreen Lotion

Active Ingredients

Avobenzone 3%, Homosalate 10%, Octocrylene 6%

Purpose

Sunscreen

Uses

- Helps prevent sunburn
- If used as directed with other sun protection measures (see Directions), decreases the risk of skin cancer and early skin aging caused by the sun.

Warnings

For external use only.

Do not use on damaged or broken skin. When using this product keep out of eyes. Rinse eyes with water to remove.

Stop use and ask a doctor if rash or irritation develops and lasts.

PREGNANCY OR BREAST FEEDING

Ask a health professional before use.

Keep Out of Reach of Children.

If product is swallowed, get medical help or contact a Poison Control Center right away.

Directions

Apply liberally 15 minutes before sun exposure. Reapply:

- after 80 minutes of swimming or sweating
- immediately after towel drying
- at least every 2 hours

Sun protection measures: spending time n the sun increases your risk of skin cancer and early skin aging. To decrease risk, regularly use a sunscreen with broad spectrum SPF of 15 or higher and other sun protection measure including:

- limit time in the sun, especially from 10 am to 2 pm
- wear long-sleeved shirts, pants, hats, and sunglasses.
- Children under 6 months: ask a doctor.

Inactive Ingredients

Aluminum Starch Octenylsuccinate, Butyloctyl Salicylate, Carbomer, Dimethicone, Disodium EDTA, Ethylhexylglycerin, Phenoxyethanol, Polyglceryl-3 Distearate, Sorbitan Isostearate, Sorbitol, Stearic Acid, Triethanolamine, VP/Eicosene Copolymer, Water.